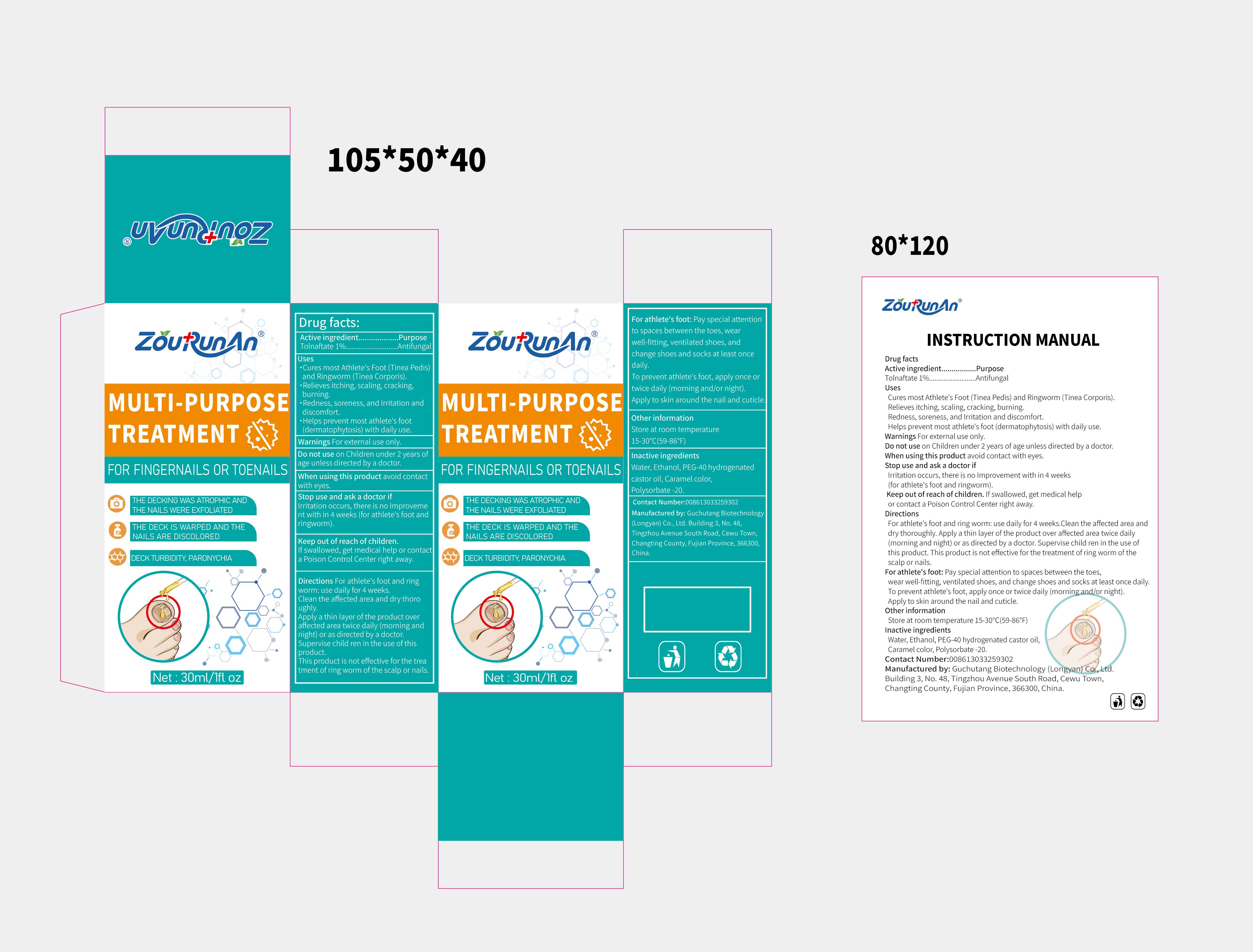 DRUG LABEL: zourunan MULTI-PURPOS TREATMENT
NDC: 87083-001 | Form: LIQUID
Manufacturer: Guchutang Biotechnology (Longyan) Co., Ltd
Category: otc | Type: HUMAN OTC DRUG LABEL
Date: 20251022

ACTIVE INGREDIENTS: TOLNAFTATE 1 g/100 mL
INACTIVE INGREDIENTS: CARAMEL; POLYOXYL 40 HYDROGENATED CASTOR OIL; POLYSORBATE 20; ALCOHOL; WATER

87083-001

Active Ingredient

Tolnaftate 1%

Purpose

Antifungal

Use

Cures most Athlete's Foot (Tinea Pedis) and Ringworm (Tinea Corporis).
Relieves itching, scaling, cracking, burning.
redness, soreness, and Irritation and discomfort.
Helps prevent most athlete's foot (dermatophytosis) with daily use.

Warnings

For external use only.

Do not use

on Children under 2 years of age unless directed by a doctor.

When Using

When using this product avoid contact with eyes.

Stop Use

Irritation occurs, there is no Improvement with in 4 weeks (for athlete's foot and ringworm).

Ask Doctor

Irritation occurs, there is no Improvement with in 4 weeks (for athlete's foot and ringworm).

Keep Out Of Reach Of Children

If swallowed, get medical help or contact a Poison Control Center right away.

Directions

For athlete's foot and ring worm: use daily for 4 weeks.

Clean the affected area and dry thoroughly.

Apply a thin layer of the product over affected area twice daily(morning and night) or as directed by a doctor. Supervise child ren in the use of this product.

This product is not effective for the treatment of ring worm of the scalp or nails.

Other information

Store at room temperature 15-30℃(59-86℉)

Inactive ingredients

Water, Ethanol, PEG-40 hydrogenated castor oil, Caramel color, Polysorbate -20.